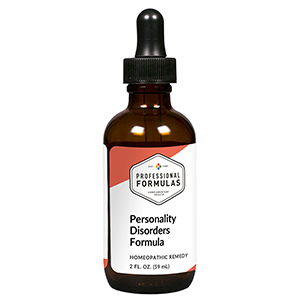 DRUG LABEL: Personality Disorders Formula
NDC: 63083-2112 | Form: LIQUID
Manufacturer: Professional Complementary Health Formulas
Category: homeopathic | Type: HUMAN OTC DRUG LABEL
Date: 20190815

ACTIVE INGREDIENTS: LEUZEA RHAPONTICA ROOT 3 [hp_X]/59 mL; PODOPHYLLUM 6 [hp_X]/59 mL; RHEUM PALMATUM ROOT 6 [hp_X]/59 mL; THUJA OCCIDENTALIS LEAF 6 [hp_X]/59 mL; SOLIDAGO VIRGAUREA FLOWERING TOP 6 [hp_X]/59 mL
INACTIVE INGREDIENTS: ALCOHOL; WATER

C112

ACTIVE INGREDIENTS

Lou-Lu 3X
Pa-Chiao-Lien 6X
Ta-Huang 6X
Tse-Po-Yeh 6X, 12X
Liu-Huang 6X, 12X, 30X, 50X

QUESTIONS

Professional Formulas

PO Box 2034 Lake Oswego, OR 97035

INDICATIONS

For the temporary relief of impulsive behavior, irritability, anxiousness, or mood swings.*

PURPOSE

*Claims based on traditional homeopathic practice, not accepted medical evidence. Not FDA evaluated.

WARNINGS

Severe or persistent symptoms may be serious. Consult a doctor promptly. Keep out of the reach of children. In case of overdose, get medical help or contact a poison control center right away. If pregnant or breastfeeding, ask a healthcare professional before use.

Keep out of the reach of children.

PREGNANCY OR BREAST FEEDING

If pregnant or breastfeeding, ask a healthcare professional before use.

DIRECTIONS

Place drops under tongue 30 minutes before/after meals. Adults and children 12 years and over: Take 10 drops up to 3 times per day. Consult a physician for use in children under 12 years of age.

OTHER INFORMATION

Tamper resistant. If seal is broken, do not use. After opening, close container tightly and store at room temperature away from heat.

INACTIVE INGREDIENTS

20% ethanol, purified water.

LABEL

Est 1985

Professional Formulas

Complementary Health

Personality Disorders Formula

Homeopathic Remedy

2 FL. OZ. (59 mL)